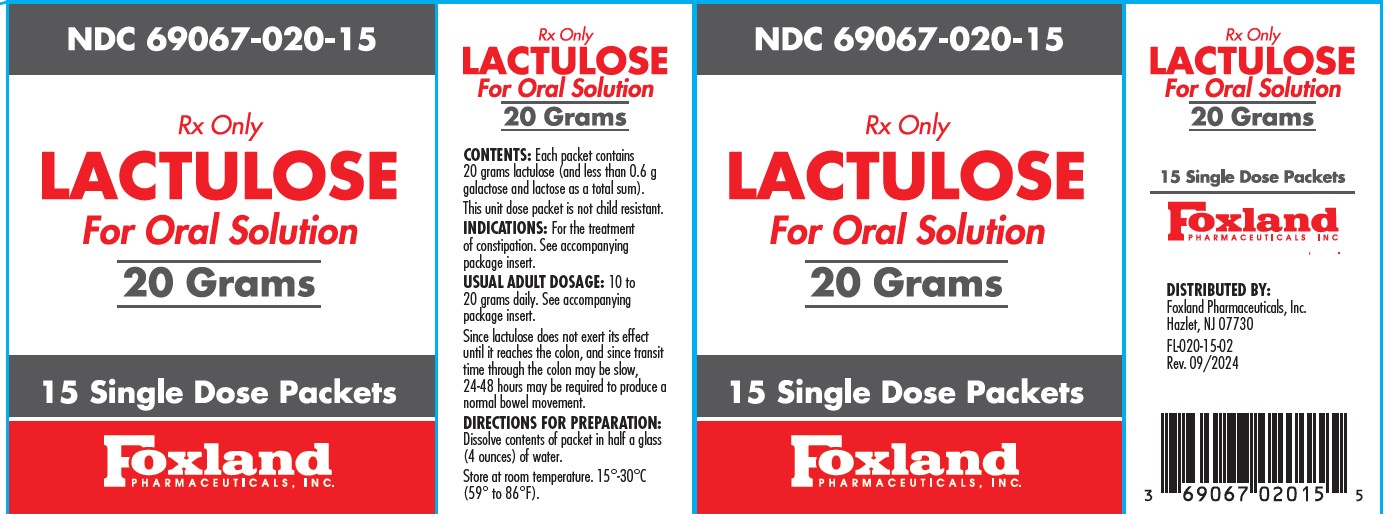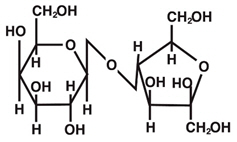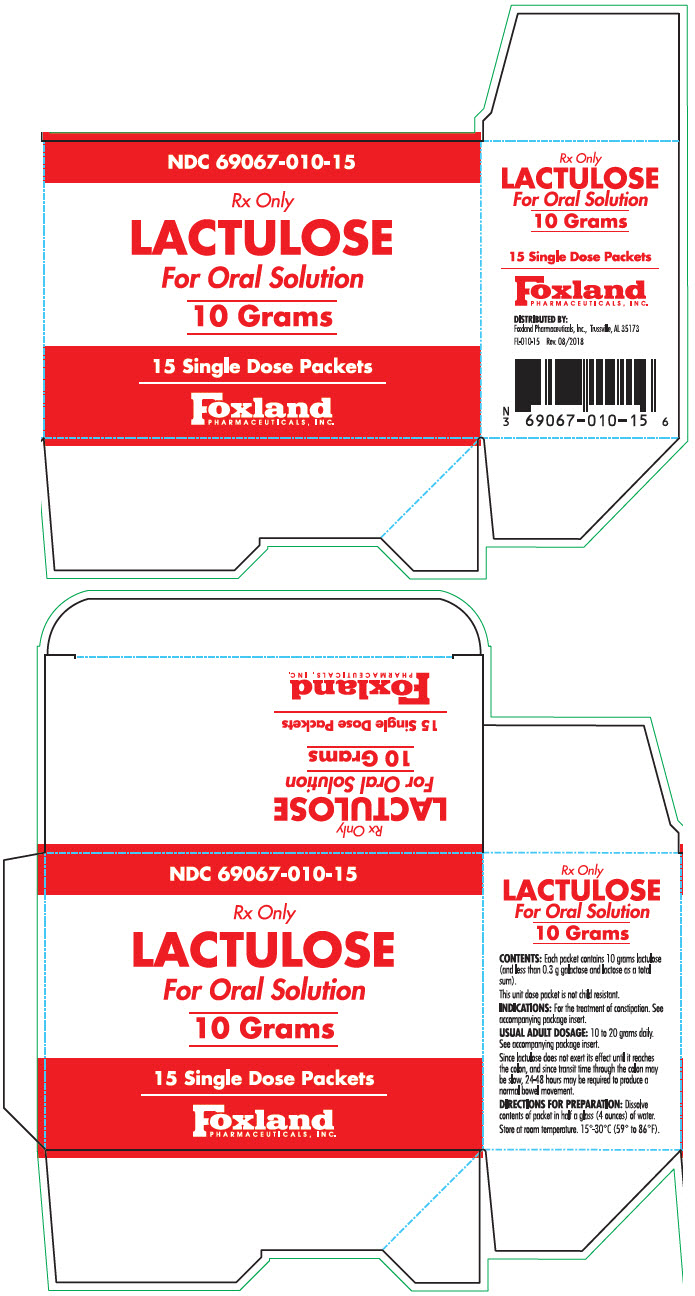 DRUG LABEL: Lactulose
NDC: 69067-020 | Form: SOLUTION
Manufacturer: Foxland Pharmaceuticals, Inc.
Category: prescription | Type: HUMAN PRESCRIPTION DRUG LABEL
Date: 20251216

ACTIVE INGREDIENTS: LACTULOSE 20 g/20 g

LACTULOSE
For Oral Solution

Foxland Pharmaceuticals Inc.

Rx Only

DESCRIPTION

LACTULOSE For Oral Solution is a synthetic disaccharide in the form of crystals for reconstitution prior to use for oral administration Each 10 g of lactulose contains less than 0.3 g galactose and lactose as a total sum. The pH range is 3.0 to 7.0.

Lactulose is a colonic acidiﬁer which promotes laxation.

The chemical name for lactulose is 4-O-β-D-Galactopyranosyl-D-fructofuranose. It has the following structural formula:

The molecular formula is C12H22O11. The molecular weight is 342.30.
It is freely soluble in water.

CLINICAL PHARMACOLOGY

LACTULOSE is poorly absorbed from the gastro-intestinal tract and no enzyme capable of hydrolysis of this disaccharide is present in human gastrointestinal tissue. As a result, oral doses of lactulose reach the colon virtually unchanged. In the colon, lactulose is broken down primarily to lactic acid, and also to small amounts of formic and acetic acids, by the action of colonic bacteria, which results in an increase in osmotic pressure and slight acidiﬁcation of the colonic contents. This in turn causes an increase in stool water content and softens the stool.

Since lactulose does not exert its effect until it reaches the colon, and since transit time through the colon may be slow, 24 to 48 hours may be required to produce desired bowel movement.

Lactulose given orally to man and experimental animals resulted in only small amounts reaching the blood. Urinary excretion has been determined to be 3% or less and is essentially complete within 24 hours.

INDICATIONS AND USAGE

LACTULOSE For Oral Solution is indicated for the treatment of constipation. In patients with a history of chronic constipation, lactulose therapy increases the number of bowel movements per day and the number of days on which bowel movements occur.

CONTRAINDICATIONS

Since LACTULOSE For Oral Solution contains galactose (less than 0.3 g/10 g as a total sum with lactose), it is contraindicated in patients who require a low galactose diet.

WARNINGS

A theoretical hazard may exist for patients being treated with lactulose who may be required to undergo electrocautery procedures during proctoscopy or colonoscopy. Accumulation of H2gas in signiﬁcant concentration in the presence of an electrical spark may result in an explosive reaction. Although this complication has not been reported with lactulose, patients on lactulose therapy undergoing such procedures should have a thorough bowel cleansing with a non-fermentable solution. Insufﬂation of CO2as an additional safeguard may be pursued but is considered to be a redundant measure.

PRECAUTIONS

General

Since LACTULOSE For Oral Solution contains galactose and lactose (less than 0.3 g/10 g as a total sum), it should be used with caution in diabetics.

Information for Patients

In the event that an unusual diarrheal condition occurs, contact your physician.

Laboratory Tests

Elderly, debilitated patients who receive lactulose for more than six months should have serum electrolytes (potassium, chloride, carbon dioxide) measured periodically.

Drug Interactions

Results of preliminary studies in humans and rats suggest that nonabsorbable antacids given concurrently with lactulose may inhibit the desired lactulose-induced drop in colonic pH. Therefore, a possible lack of desired effect of treatment should be taken into consideration before such drugs are given concomitantly with lactulose.

Carcinogenesis, Mutagenesis, Impairment of Fertility

There are no known human data on long-term potential for carcinogenicity, mutagenicity, or impairment of fertility.

There are no known animal data on long-term potential for mutagenicity.

Administration of lactulose syrup in the diet of mice for 18 months in concentrations of 3 and 10 percent (v/w) did not produce any evidence of carcinogenicity.

In studies in mice, rats, and rabbits, doses of lactulose syrup up to 6 or 12 mL/kg/day produced no deleterious effects in breeding, conception, or parturition.

Pregnancy

Teratogenic Effects

Reproduction studies have been performed in mice, rats, and rabbits at doses up to 3 or 6 times the usual human oral dose and have revealed no evidence of impaired fertility or harm to the fetus due to lactulose. There are, however, no adequate and well-controlled studies in pregnant women. Because animal reproduction studies are not always predictive of human response, this drug should be used during pregnancy only if clearly needed.

Nursing Mothers

It is not known whether this drug is excreted in human milk. Because many drugs are excreted in human milk, caution should be exercised when lactulose is administered to a nursing woman.

Pediatric Use

Safety and effectiveness in pediatric patients have not been established.

ADVERSE REACTIONS

Precise frequency data are not available.

Initial dosing may produce flatulence and intestinal cramps, which are usually transient. Excessive dosage can lead to diarrhea with potential complications such as loss of ﬂuids, hypokalemia, and hypernatremia.

Nausea and vomiting have been reported.

OVERDOSAGE

Signs and Symptoms

There have been no reports of accidental overdosage. In the event of overdosage, it is expected that diarrhea and abdominal cramps would be the major symptoms. Medication should be terminated.

Oral LD50

The acute oral LD50of the drug is 48.8 mL/kg in mice and greater than 30 mL/kg in rats.

Dialysis

Dialysis data are not available for lactulose. Its molecular similarity to sucrose, however, would suggest that it should be dialyzable.

DOSAGE AND ADMINISTRATION

The usual adult dosage is 10 g to 20 g of lactulose daily. The dose may be increased to 40 g daily if necessary. Twenty-four to 48 hours may be required to produce a normal bowel movement.

DIRECTIONS FOR PREPARATION

Dissolve contents of packet in half a glass (4 ounces) of water.

When Lactulose For Oral Solution is dissolved in water, the resulting solution may be colorless to a slightly pale yellow color.

HOW SUPPLIED

LACTULOSE For Oral Solution is available in single dose packets of 10 g (NDC 69067-010-15) andd single dose packets of 20 g (NDC 69067020-15). The packets are supplied as follows:

NDC 69067-010-15 (Carton of fifteen 10 g packets)

NDC 69067-020-14 (carton of fifteen 20g paclets)

STORAGE AND HANDLING

STORE AT ROOM TEMPERATURE, 15°-30°C (59°-86°F).

To report SUSPECTED ADVERSE REACTIONS, contact Foxland Pharmaceuticals Inc. at 1-844-700-5011 or FDA at 1-800-FDA-1088 or www.fda.gov/medwatch.

Distributed by:
FOXLAND PHARMACEUTICALS, INC.
Hazlet, NJ 07730

Issued: October 2024

PRINCIPAL DISPLAY PANEL - 10 Gram Packet Carton

NDC 69067-010-15

Rx Only

Lactulose 10 g packets

For Oral Solution

Fifteen Single Dose Packets

Foxland Pharmaceuticals, Inc

PACKAGE LABEL

NDC 69067-020-15

Rx Only

Lactulose, 20 g Packets

Fifteen single dose packets

Foxland, Pharmaceuticals, Inc.